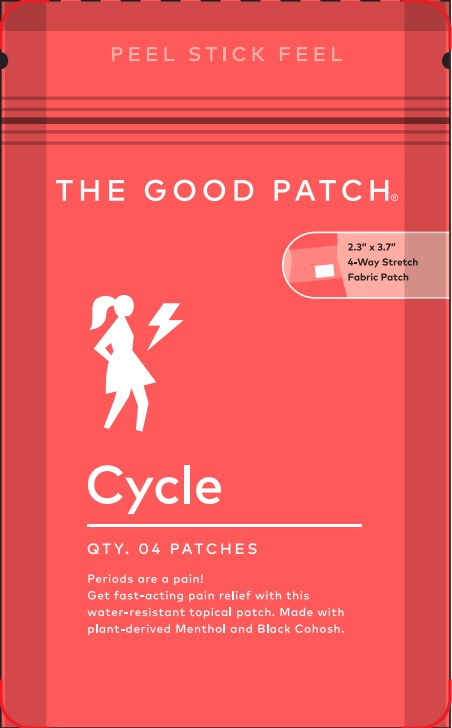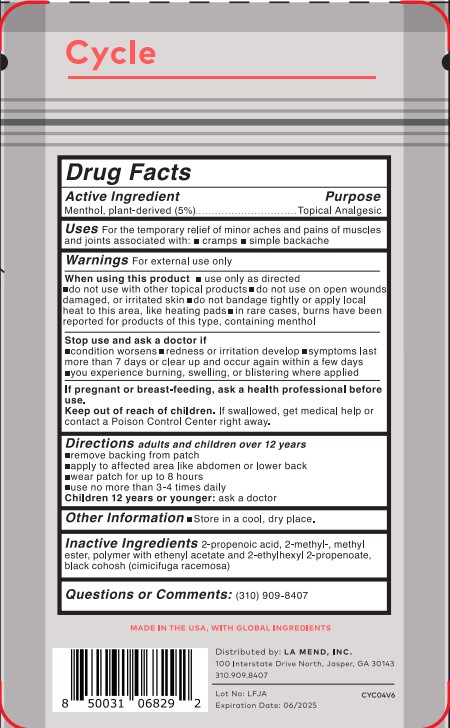 DRUG LABEL: Cycle
NDC: 72587-001 | Form: PATCH
Manufacturer: La Mend, Inc.
Category: otc | Type: HUMAN OTC DRUG LABEL
Date: 20231207

ACTIVE INGREDIENTS: MENTHOL 5 g/100 g
INACTIVE INGREDIENTS: 1,1'-((1-METHYL-1,2-ETHANEDIYL)2-PROPENOIC ACID, BIS(OXY(1-METHYL-2,1-ETHANEDIYL))) ESTER

Active Ingredient(s)

Menthol (5%)

Purpose

Topical Analgesic

Use

For the temporary relief of minor aches and pains of muscles and joins associated with:

- cramps
- simple backache

Warnings

For external use only.

When using this product

- use only as directed
- do not use with other topical products
- do not use on open wounds, damaged or irritated skin
- do not bandage tightly or apply local heat to this area, like heating pads
- in rare cases, burns have been reported for products of this type, containing menthol

Stop use and ask a doctor if

- confiditon worsens
- redness or irritation develop
- symptoms last more than 7 days or clear up and occur again within a few days
- you experience burning, swelling, or blistering where applied

PREGNANCY OR BREAST FEEDING

If pregnant or breast-feeding, ask a health professional before use.

Keep out of reach of children. If swallowed, get medical help or contact a Poison Control Center right away.

Directions

Adults and children over 12 years

- remove backing from patch
- apply patch to affected area like abdomen or lower back
- wear patch for up to 8 hours
- use no more than 3-4 times daily

Children 12 years or younger: ask a doctor

Other information

- Store in a cool, dry place.

Inactive ingredients

Inactive Ingredients: 2-propenoic acid, 2-methyl-, methyl ester, polymer with ethenyl acetate and 2-ethylhexyl 2-propenoate, black cohosh (cimicifuga racemosa)

RECENT MAJOR CHANGES

Directions (December 2023)

Package Label - Principal Display Panel

THE GOOD PATCH

2.3" x 3.7"

4-Way Stretch

Fabric Patch

Cycle

QTY. 04 PATCHES

Periods are a pain!

Get fast-acting pain relief with this water-resistant topical patch. Made with plant-derived Menthol and Black Cohosh.